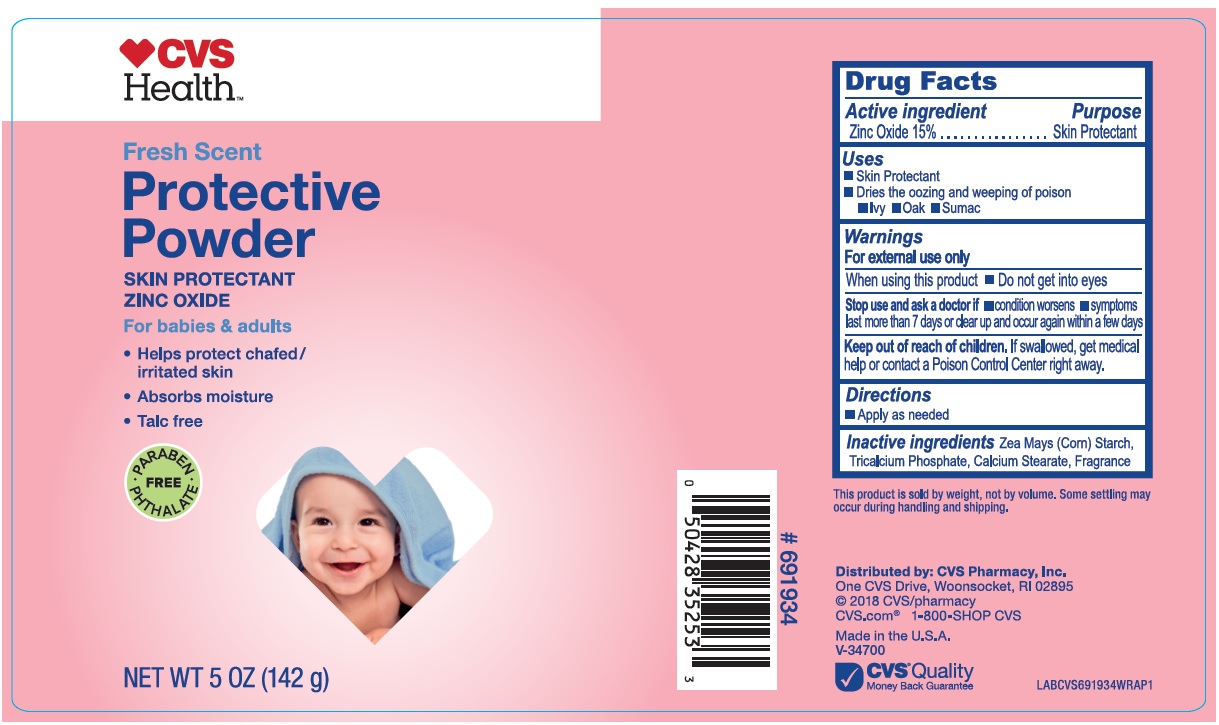 DRUG LABEL: Protective Powder
NDC: 42669-233 | Form: POWDER
Manufacturer: Davion, Inc.
Category: otc | Type: HUMAN OTC DRUG LABEL
Date: 20240228

ACTIVE INGREDIENTS: ZINC OXIDE 15 g/142 g
INACTIVE INGREDIENTS: TRICALCIUM PHOSPHATE; ZEA MAYS SUBSP. MAYS WHOLE; CALCIUM STEARATE

Drug Facts

Active Ingredients

Zinc Oxide 15%

Purpose

Skin Protectant

Uses

- Skin Protectant
- Dries the oozing and weeping of poison
- Ivy
- Oak
- Sumac

Warnings

For external use only.

When using this product

- Do not get into eyes

Stop use and ask a doctor

- if condition worsens
- symptoms last more than 7 days or clear up and occur again within a few days

Keep out of reach of children

If swallowed, get medical help or contact a Poison Control Center right away.

Directions

- Apply as needed

Inactive ingredients

Zea Mays (Corn) Starch, Tricalcium Phosphate, Calcium Stearate, Fragrance

Principal Display Panel

CVS Health

Fresh Scent

Protective

Powder

SKIN PROTECTANT

ZINC OXIDE

For babies & adults

- Helps protect chafed/irritated skin
- Absorbs moisture
- Talc free

NET WT 5 OZ (142g)